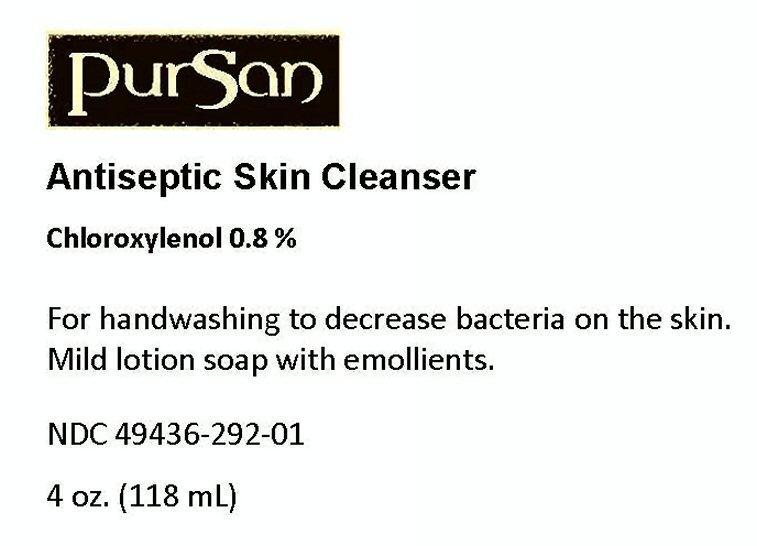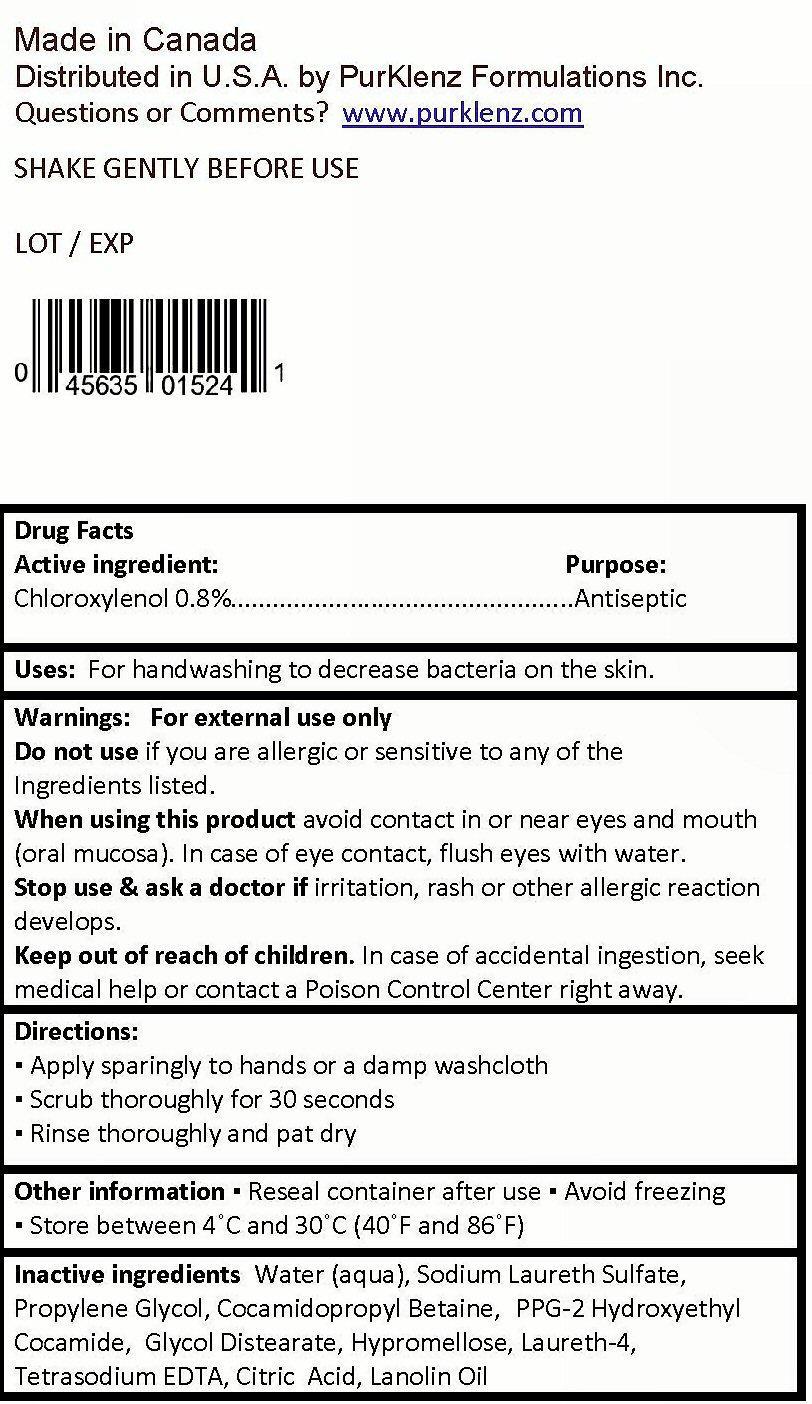 DRUG LABEL: PurSan
NDC: 49436-292 | Form: LOTION
Manufacturer: PurKlenz Formulations Inc.
Category: otc | Type: HUMAN OTC DRUG LABEL
Date: 20191105

ACTIVE INGREDIENTS: CHLOROXYLENOL 0.08 mg/100 mL
INACTIVE INGREDIENTS: WATER; SODIUM LAURETH-3 SULFATE; PROPYLENE GLYCOL; COCAMIDOPROPYL BETAINE; PPG-2 HYDROXYETHYL COCAMIDE; GLYCOL DISTEARATE; HYPROMELLOSES; LAURETH-4; EDETATE SODIUM; CITRIC ACID MONOHYDRATE; LANOLIN OIL

Active ingredient:

Drug Facts

Active ingredient:

Chloroxylenol 0.8%

Purpose:

Antiseptic

Keep out of reach of children. In case of accidental ingestion, seek medical help or contact a Poison Control Center right away.

Uses:

For handwashing to decrease bacteria on the skin.

Warnings:

For external use only

Do not use if you are allergic or sensitive to any of the ingredients listed.

When using this product avoid contact in or near eyes and mouth (oral mucosa). In case of eye contact, flush eyes with water.

Stop use and ask a doctor if irritation, rash or other allergic reaction develops.

Directions:

- Apply sparingly to hands or a damp washcloth
- Scrub thoroughly for 30 seconds
- Rinse thoroughly and pat dry

Other information

- reseal container after use
- Avoid freezing
- Store between 4 degrees C and 30 degrees C (40 degrees F and 86 degrees F)

Inactive ingredients

Water (aqua), Sodium Laureth Sulfate, Propylene Glycol, Cocamidopropyl Betadine, PPG-2 Hydroxyethyl Cocamide, Glycol Distearate, Hypromellose, Laureth-4, Tetrasodium EDTA, Citric Acid, Lanolin Oil

Product Label

PurSan

Antiseptic Skin Cleanser

Chloroxylenol 0.8%

For handwashing to decrease bacteria on the skin.
Mild lotion soap with emollients.

NDC 49436-292-01

4 oz. (118 mL)

Made in Canada
Distributed in the U.S.A. by PurKlenz Formulations Inc.
Questions or comments? www.purklenz.com

SHAKE GENTLY BEFORE USE

LOT / EXP

res